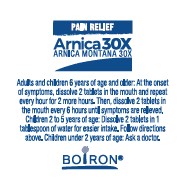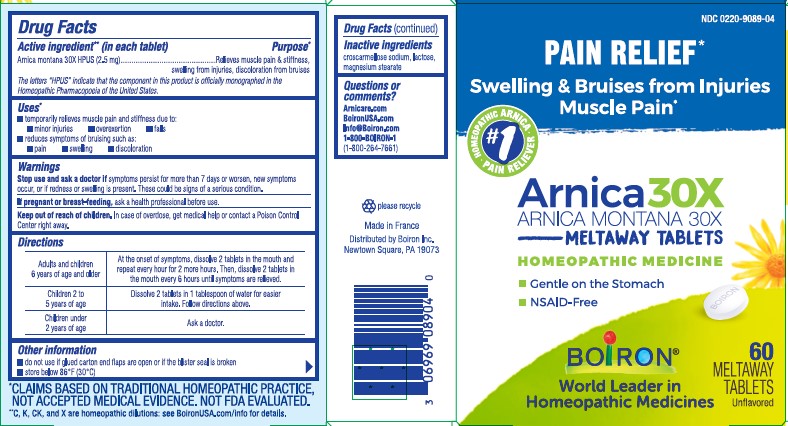 DRUG LABEL: ARNICA
NDC: 0220-9089 | Form: TABLET
Manufacturer: Boiron
Category: homeopathic | Type: HUMAN OTC DRUG LABEL
Date: 20230929

ACTIVE INGREDIENTS: ARNICA MONTANA 30 [hp_X]/1 1
INACTIVE INGREDIENTS: MAGNESIUM STEARATE; CROSCARMELLOSE SODIUM; LACTOSE, UNSPECIFIED FORM

Arnica 30X Tablets

Active ingredients** (in each tablet)

Arnica montana 30X HPUS (2.5 mg)

The letters HPUS indicate that the component in this product is officially monographed in the Homeopathic Pharmacopoeia of the United States.

Purpose*

Relieves muscle pain & stiffness, swelling from injuries, discoloration from bruises

Uses*

temporarily relieves muscle pain and stiffness due to: minor injuries overexertion falls
reduces symptoms of bruising such as: pain swelling discoloration

Stop use and ask a doctor if symptoms persist for more than 7 days or worsen, new symptoms occur, or if redness or swelling is present. These could be signs of a serious condition.

PREGNANCY OR BREAST FEEDING

If pregnant or breast-feeding, ask a health professional before use.

Keep out of reach of children. In case of overdose, get medical help or contact a Poison Control Center right away.

DOSAGE AND ADMINISTRATION

Adults and children 6 years for age and older - At the onset of symptoms, dissolve 2 tablets in the mouth and repeat every hour for 2 more hours. Then, dissolve 2 tablets in the mouth every 6 hours until symptoms are relieved.

Children 2 to 5 years of age: Dissolve 2 tablets in 1 tablespoon of water for easier intake. Follow directions above.

Children under 2 years of age: Ask a doctor.

INACTIVE INGREDIENT

croscarmellose sodium, lactose, magnesium stearate

Questions or comments?

Arnicare.com

BoironUSA.com

Info@Boiron.com

1-800-BOIRON-1

(1-800-264-7661)

Made in France

Distributed by Boiron Inc.

Newtown Square, PA 19073

do not use if glued carton ends flaps are open or if the blister seal is broken

store below 86°F (30°C)

PAIN RELIEF*

Swelling & Bruises from Injuries Muscle Pain*

60 Meltaway Tablets, unflavored

Gentle on the stomach

NSAID-Free

No Known Drug Interactions

Non-Drowsy

Meltaway Tablets Require No Food or Water

*CLAIMS BASED ON TRADITIONAL HOMEOPATHIC PRACTICE NOT ACCEPTED MEDICAL EVIDENCE. NOT FDA EVALUATED.
**C,K,CK, and X are homeopathic dilutions: see BoironUSA.com/info for details.